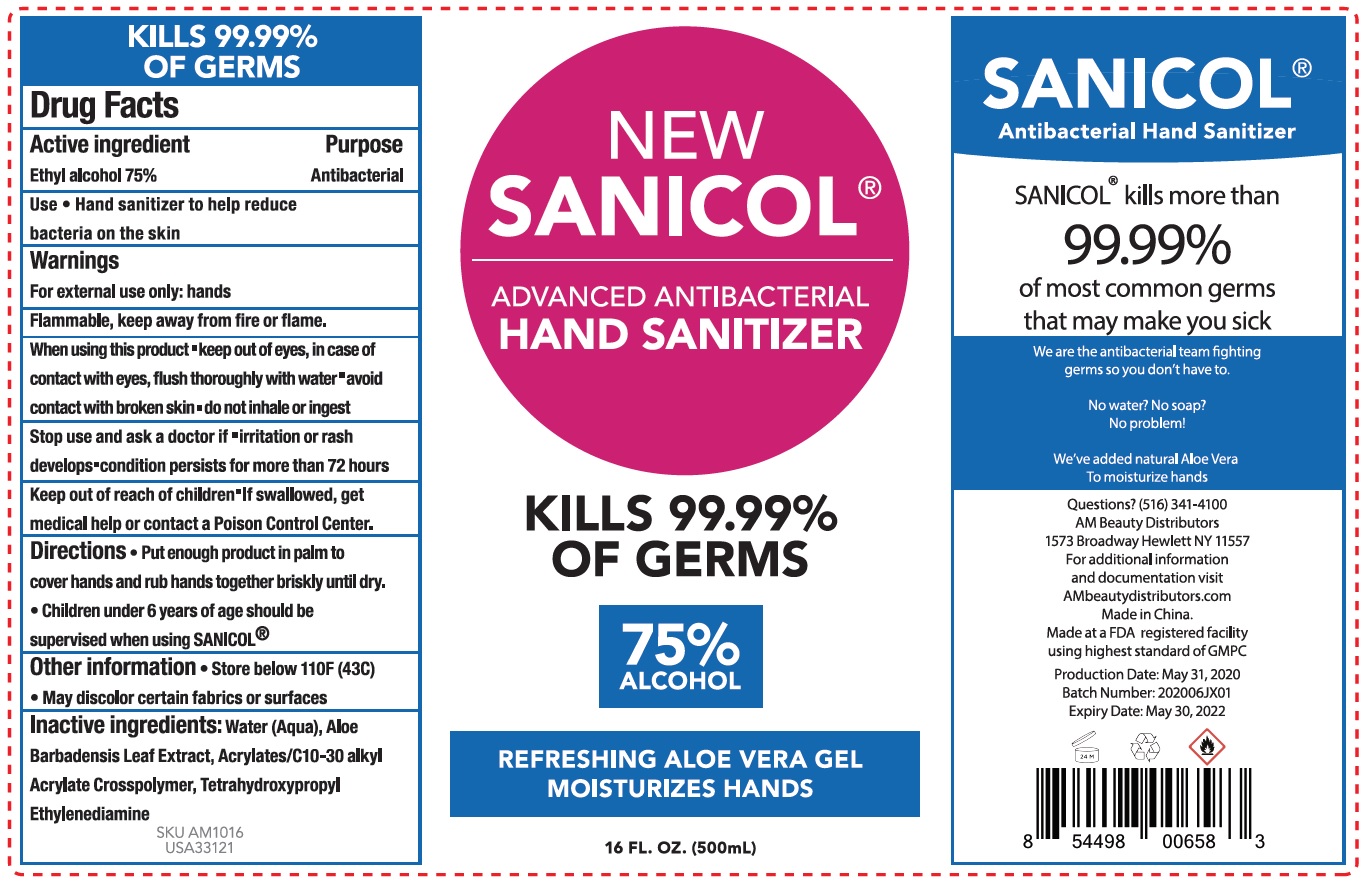 DRUG LABEL: NEW SANICOL ADVANCED ANTIBACTERIAL HAND SANITIZER
NDC: 79254-019 | Form: GEL
Manufacturer: AM Beauty Distributors Inc.
Category: otc | Type: HUMAN OTC DRUG LABEL
Date: 20200629

ACTIVE INGREDIENTS: ALCOHOL 0.75 mL/1 mL
INACTIVE INGREDIENTS: WATER; ALOE VERA LEAF; CARBOMER INTERPOLYMER TYPE A (ALLYL SUCROSE CROSSLINKED); EDETOL

NEW SANICOL ADVANCED ANTIBACTERIAL HAND SANITIZER

Active ingredient

Ethyl alcohol 75%

Purpose

Antibacterial

Use

- Hand sanitizer to help reduce bacteria on the skin

Warnings

For external use only: hands

Flammable, keep away from fire or flame.

When using this product

- keep out of eyes, in case of contact with eyes, flush thoroughly with water
- avoid contact with broken skin
- do not inhale or ingest

Stop use and ask a doctor if

- irritation or rash develops
- condition persists for more than 72 hours

Keep out of reach of children

- If swallowed, get medical help or contact a Poison Control Center.

Directions

- Put enough product in palm to cover hands and rub hands together briskly until dry.
- Children under 6 years of age should be supervised when using SANICOL®

Other information

- Store below 110F (43C)
- May discolor certain fabrics or surfaces

Inactive ingredients:

Water (Aqua), Aloe Barbadensis Leaf Extract, Acrylates/C10-30 alkyl Acrylate Crosspolymer, Tetrahydroxypropyl Ethylenediamine